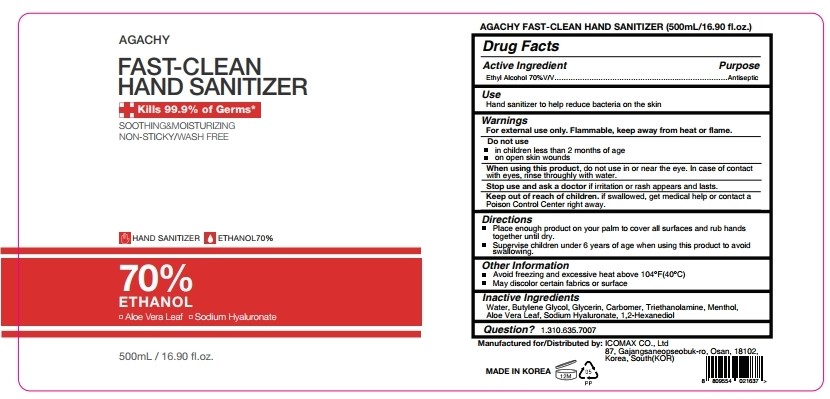 DRUG LABEL: AGACHY FAST CLEAN HAND SANITIZER
NDC: 77201-002 | Form: GEL
Manufacturer: ICOMAX Co., Ltd.
Category: otc | Type: HUMAN OTC DRUG LABEL
Date: 20200528

ACTIVE INGREDIENTS: ALCOHOL 70 mL/100 mL
INACTIVE INGREDIENTS: HYALURONATE SODIUM; 1,2-HEXANEDIOL; GLYCERIN; BUTYLENE GLYCOL; WATER; LEVOMENTHOL; CARBOMER HOMOPOLYMER TYPE B (ALLYL PENTAERYTHRITOL CROSSLINKED); TROLAMINE; ALOE VERA LEAF

This is a hand sanitizer manufactured according to the Temporary Policy for Preparation of Certain Alcohol-Based Hand Sanitizer Products During the Public Health Emergency (CoViD-19); Guidance for Industry.

The hand sanitizer is manufactured using only the following United States Pharmacopoeia (USP) grade ingredients in the preparation of the product (percentage in final product formulation) consistent with World Health Organization (WHO) recommendations:

1. Alcohol (ethanol) (USP or Food Chemical Codex (FCC) grade) (80%, volume/volume (v/v)) in an aqueous solution denatured according to Alcohol and Tobacco Tax and Trade Bureau regulations in 27 CFR part 20.
2. Glycerol (1.45% v/v).
3. Hydrogen peroxide (0.125% v/v).
4. Sterile distilled water or boiled cold water.

The firm does not add other active or inactive ingredients. Different or additional ingredients may impact the quality and potency of the product.

Active Ingredient(s)

Alcohol 70% v/v. Purpose: Antiseptic

Purpose

Antiseptic, Hand Sanitizer

Use

Hand Sanitizer to help reduce bacteria on the skin.

Warnings

For external use only. Flammable. Keep away from heat or flame.

When using this product do not use in or near the eye. In case of contact with eyes, rinse thoroughly with water.

Stop use and ask a doctor if irritation or rash appears and lasts.

Keep out of reach of children. If swallowed, get medical help or contact a Poison Control Center right away.

Directions

- Place enough product on your palm to cover all surfaces and rub hands together until dry.
- Supervise children under 6 years of age when using this product to avoid swallowing.

Other information

- Avoid freezing and excessive heat above 40C (104F)
- May discolor certain fabrics or surface

Inactive ingredients

Water, Butylene Glycol, Glycerin, Carbomer, Triethanolamine, Menthol, Aloe Barbadensis Leaf, Sodium Hyaluronate, 1,2-Hexanediol

Package Label - Principal Display Panel

500 mL NDC: 77201-002-50